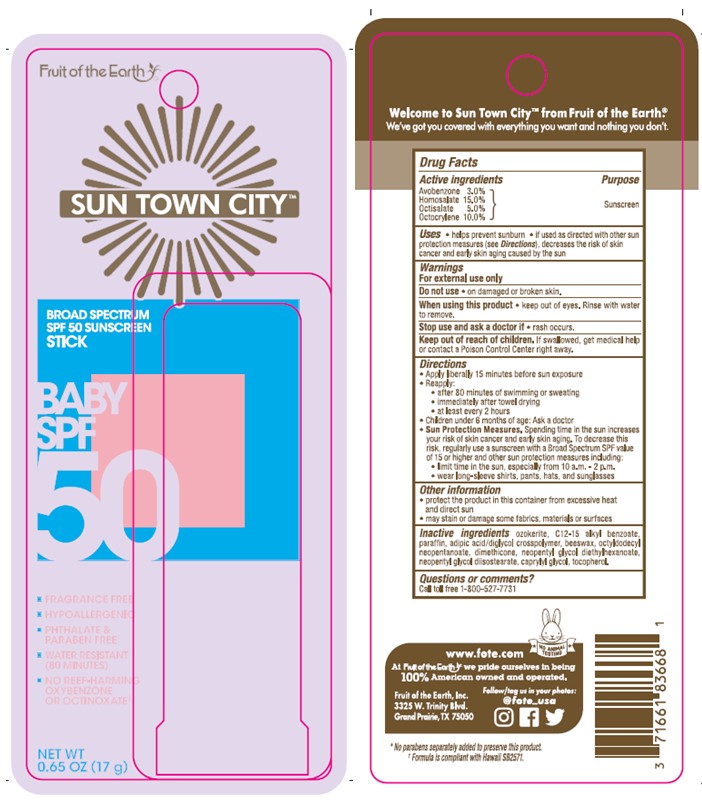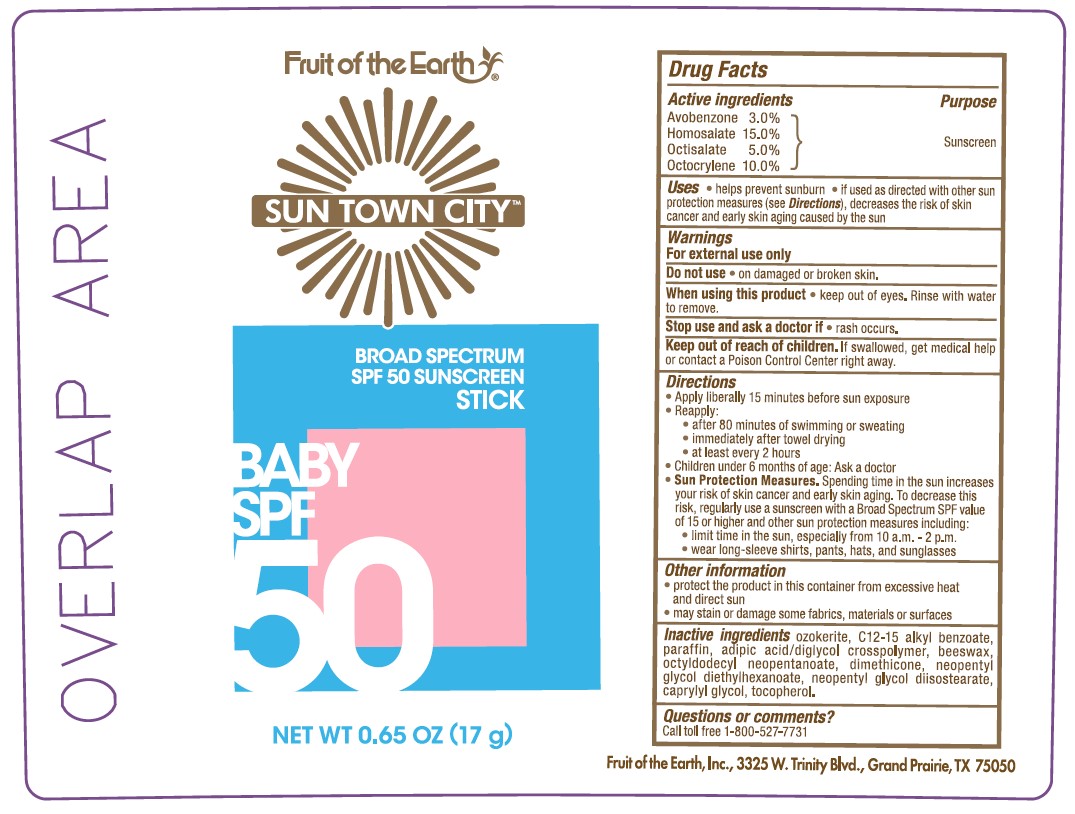 DRUG LABEL: Fruit of the Earth Sun Town City Baby SPF 50 Sunscreen
NDC: 62217-077 | Form: STICK
Manufacturer: Fruit of the Earth, Inc.
Category: otc | Type: HUMAN OTC DRUG LABEL
Date: 20241017

ACTIVE INGREDIENTS: AVOBENZONE 30 mg/1 g; HOMOSALATE 150 mg/1 g; OCTISALATE 50 mg/1 g; OCTOCRYLENE 100 mg/1 g
INACTIVE INGREDIENTS: ADIPIC ACID/DIGLYCOL CROSSPOLYMER (20000 MPA.S); WHITE WAX; ALKYL (C12-15) BENZOATE; CAPRYLYL GLYCOL; DIMETHICONE; .ALPHA.-TOCOPHEROL, DL-; NEOPENTYL GLYCOL DIETHYLHEXANOATE; NEOPENTYL GLYCOL DIISOSTEARATE; OCTYLDODECYL NEOPENTANOATE; CERESIN; PARAFFIN

Fruit of the Earth Sun Town City Baby SPF 50 Sunscreen Stick

Active ingredients

Avobenzone 3.0%, Homosalate 15.0%, Octisalate 5.0%, Octocrylene 10.0%

Purpose

Sunscreen

Uses

• helps prevent sunburn • if used as directed with other sun protection measures (see Directions), decreases the risk of skin cancer and early skin aging caused by the sun

Warnings

For external use only

Do not use

• on damaged or broken skin.

When using this product

• keep out of eyes. Rinse with water to remove.

Stop use and ask a doctor if

• rash occurs.

Keep out of reach of children.

If swallowed, get medical help or contact a Poison Control Center right away.

Directions

- Apply liberally 15 minutes before sun exposure
- Reapply:

• after 80 minutes of swimming or sweating

• immediately after towel drying

• at least every 2 hours

- Children under 6 months of age: Ask a doctor
- Sun Protection Measures. Spending time in the sun increases your risk of skin cancer and early skin aging. To decrease this risk, regularly use a sunscreen with a Broad Spectrum SPF value of 15 or higher and other sun protection measures including:

• limit time in the sun, especially from 10 a.m.-2 p.m.

• wear long-sleeved shirts, pants, hats, and sunglasses

Other information

- protect the product in this container from excessive heat and direct sun
- may stain or damage some fabrics, materials or surfaces

Inactive ingredients

ozokerite, C12-15 alkyl benzoate, paraffin, adipic acid/diglycol crosspolymer, beeswax, octydodecyl neopentanoate, dimethicone, neopentyl glycol diethylhexanoate, neopentyl glycol diisostearate, caprylyl glycol, tocopherol.